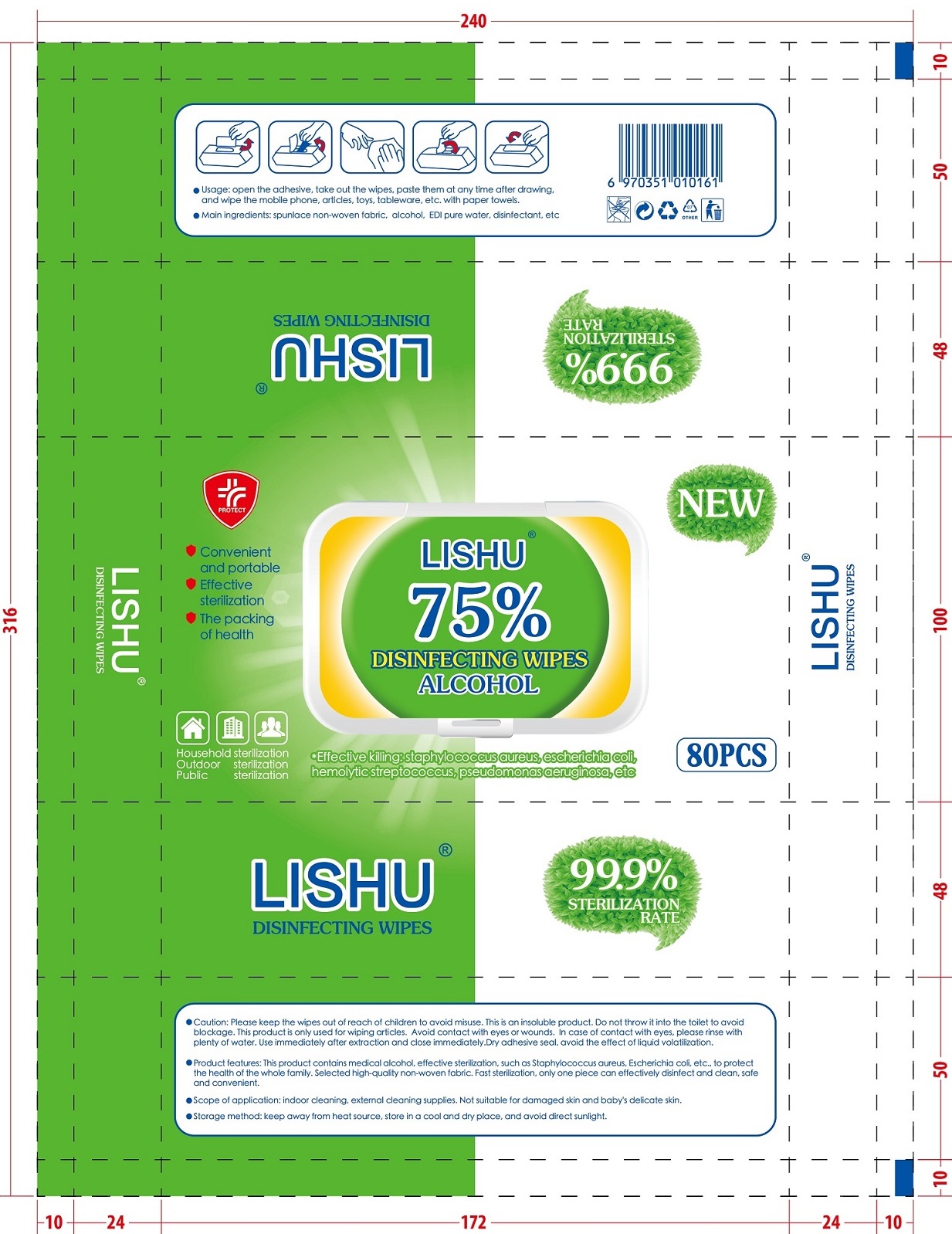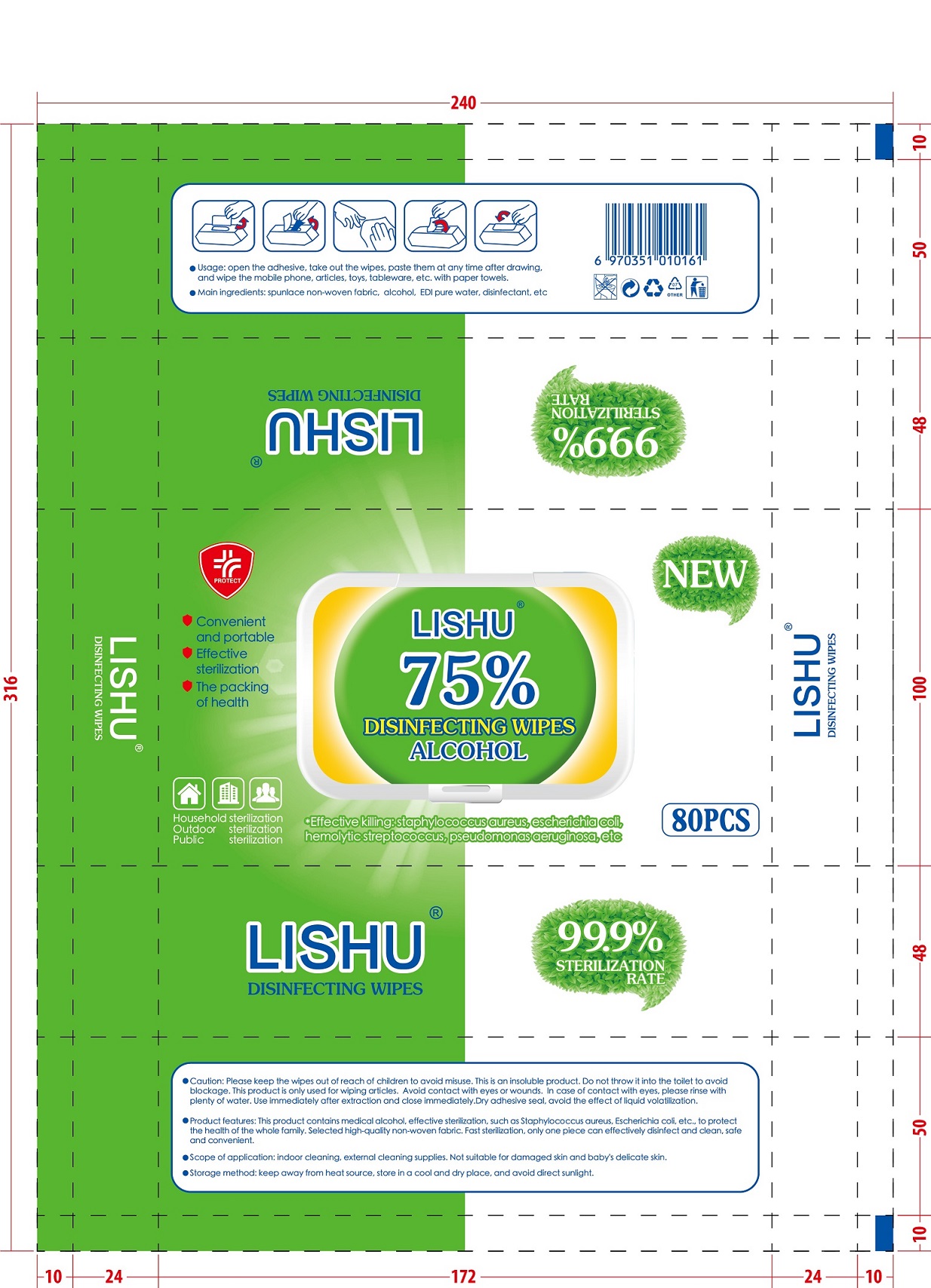 DRUG LABEL: DISINFECTANT WIPES
NDC: 52689-001 | Form: CLOTH
Manufacturer: Pujiang Shuerjie Daily Necessities Factory
Category: otc | Type: HUMAN OTC DRUG LABEL
Date: 20200709

ACTIVE INGREDIENTS: ALCOHOL 225 mL/300 1
INACTIVE INGREDIENTS: WATER; PHENOXYETHANOL

52689-001 80 cloth pujiang shuerjie

Active Ingredient(s)

Alcohol 75% v/v. Purpose: Antiseptic

Purpose

Scope of application:indoor cleaning,external cleaning suppplies.Not suitable for damaged skin and baby's delicate skin.

Use

Open the adhesive,take out the wipes,paste them at any time after drawing,and wipe the mobile phone,articles,toys,tableware,etc.with paper towels.

Warnings

Caution:

Pleace keep the wipes out of reach of children to avoid misuse.

This is an insoluble product.Do not throw it into the toilet to avoidblockage.

This product is only used for wiping articles.Avoid contact with eyes or wounds.In case of contact with eyes,please rinse withplenty of water.Use immediately after extraction and closeimmediately.Dry adhesive seal,avoid the effect of liquid volatilization.

Do not use

- in children less than 2 months of age
- on open skin wounds

When using this product keep out of eyes, ears, and mouth. In case of contact with eyes, rinse eyes thoroughly with water.
Stop use and ask a doctor if irritation or rash occurs. These may be signs of a serious condition.
Keep out of reach of children. If swallowed, get medical help or contact a Poison Control Center right away.

Stop use and ask a doctor if irritation or rash occurs. These may be signs of a serious condition.

Keep out of reach of children. If swallowed, get medical help or contact a Poison Control Center right away.

Directions

- This product contains medical alcohol,effective sterilization,such as Staphyococcus aureus,Escherichia coli,etc.,to protect the health of the whole family. Selected high-quaility non-woven fabric. Fast sterilization,only one piece can effectively disinfect and clean,safe and convenient.

Other information

- Keep away from heat source,store in a cool and dry place,and avoid direct sunlight.

Inactive ingredients

purified water USP,phenoxyethanol

Package Label - Principal Display Panel

80 cloth in 1 bag NDC:52689-001-01